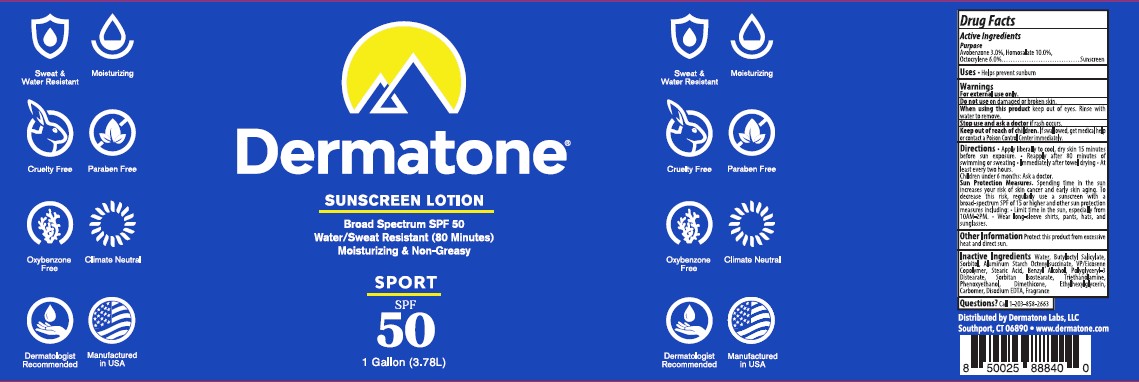 DRUG LABEL: Dermatone Sport SPF 50
NDC: 54414-027 | Form: LOTION
Manufacturer: Dermatone Labs LLC
Category: otc | Type: HUMAN OTC DRUG LABEL
Date: 20251224

ACTIVE INGREDIENTS: AVOBENZONE 3 g/100 mL; HOMOSALATE 10 g/100 mL
INACTIVE INGREDIENTS: OCTOCRYLENE 6 g/100 mL; ALUMINUM STARCH OCTENYLSUCCINATE; BENZYL ALCOHOL; BUTYLOCTYL SALICYLATE; CARBOMER; SORBITOL; DIMETHICONE; EDETATE DISODIUM; ETHYLHEXYLGLYCERIN; FRAGRANCE CLEAN ORC0600327; PHENOXYETHANOL; POLYGLYCERYL-3 DISTEARATE; SORBITAN ISOSTEARATE; STEARIC ACID; TRIETHANOLAMINE; VINYLPYRROLIDONE/EICOSENE COPOLYMER; WATER

Dermatone Sport SPF 50 Sunscreen Lotion

Active ingredients

Avobenzone 3.0%

Homosalate 10.0%

Octocrylene 6.0%

Uses

• Helps prevent sunburn, higher SPF gives more sunburn protection

WARNINGS

For external use only.

When using this product:

• keep out of eyes. Rinse with water to remove.

Stop use and ask a doctor ifrash occurs.

Keep out of reach of children.If swallowed, get medical help or contact a Poison Control Center right away

Keep out of reach of children. If swallowed, get medical help or contact a Poison Control Center right away

INACTIVE INGREDIENT

Aluminum Starch Octenylsuccinate
Benzyl Alcohol
Butyloctyl Salicylate
Carbomer
D-Glucitol
Dimethicone
Disodium EDTA
Ethylhexylglycerin
Fragrance
Phenoxyethanol
Polyglyceryl-3-Distearate
Sorbitan Isostearate
Stearic Acid
Triethanolamine
VP/Eicosene Copolymer
Water

DIRECTIONS

• Apply liberally 15 minutes before sun exposure.

• Reapply:

after 80 minutes of swimming or sweating
immediately after towel drying
at least every 2 hours

٠For sunscreen use
٠apply to all areas of the skin exposed to the sun.
٠Reapply as needed or after towel drying, swimming, or sweating.

PURPOSE

Sunscreen